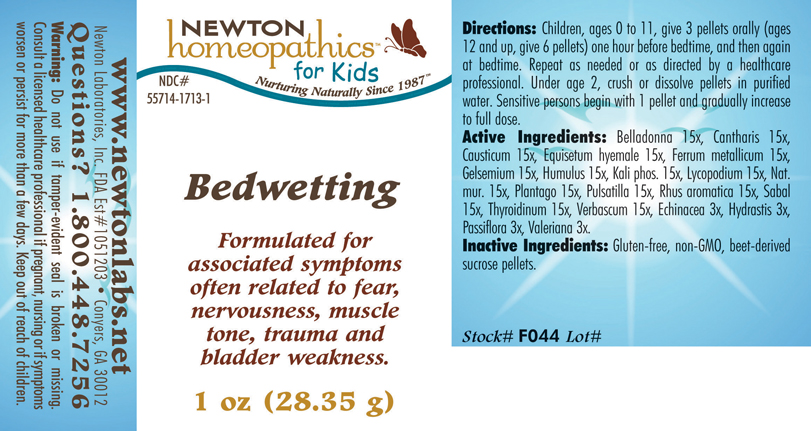 DRUG LABEL: Bedwetting 
NDC: 55714-1713 | Form: PELLET
Manufacturer: Newton Laboratories, Inc.
Category: homeopathic | Type: HUMAN OTC DRUG LABEL
Date: 20110301

ACTIVE INGREDIENTS: Atropa Belladonna 15 [hp_X]/1 g; Lytta Vesicatoria 15 [hp_X]/1 g; Causticum 15 [hp_X]/1 g; Equisetum Hyemale 15 [hp_X]/1 g; Iron 15 [hp_X]/1 g; Gelsemium Sempervirens Root 15 [hp_X]/1 g; Hops 15 [hp_X]/1 g; Potassium Phosphate, Dibasic 15 [hp_X]/1 g; Lycopodium Clavatum Spore 15 [hp_X]/1 g; Sodium Chloride 15 [hp_X]/1 g; Plantago Major 15 [hp_X]/1 g; Pulsatilla Vulgaris 15 [hp_X]/1 g; Rhus Aromatica Root Bark 15 [hp_X]/1 g; Saw Palmetto 15 [hp_X]/1 g; Thyroid, Unspecified 15 [hp_X]/1 g; Verbascum Thapsus 15 [hp_X]/1 g; Echinacea, Unspecified 3 [hp_X]/1 g; Goldenseal 3 [hp_X]/1 g; Passiflora Incarnata Flowering Top 3 [hp_X]/1 g; Valerian 3 [hp_X]/1 g
INACTIVE INGREDIENTS: Sucrose

Bedwetting

INDICATIONS & USAGE SECTION

Bedwetting Formulated for associated symptoms often related to fear, nervousness, muscle tone, trauma and bladder weakness.

DOSAGE & ADMINISTRATION SECTION

Directions: Children, ages 0 to 11, give 3 pellets orally (ages 12 and up, give 6 pellets) one hour before bedtime, and then again at bedtime. Repeat as needed or as directed by a healthcare professional. Under age 2, crush or dissolve pellets in purified water. Sensitive persons begin with 1 pellet and gradually increase to full dose.

OTC - ACTIVE INGREDIENT SECTION

Belladonna 15x, Cantharis 15x ,Causticum 15x, Equisetum hyemale 15x, Ferrum metallicum 15x, Gelsemium 15x, Humulus 15x, Kali phos. 15x, Lycopodium 15x, Nat.mur. 15x, Plantago 15x, Pulsatilla 15x, Rhus aromatica 15x,Sabal 15x, Thyroidinum 15x, Verbascum 15x, Echinacea 3x, Hydrastis 3x, Passiflora 3x, Valeriana 3x.

OTC - PURPOSE SECTION

Formulated for associated symptoms often related to fear, nervousness, muscle tone, trauma and bladder weakness.

INACTIVE INGREDIENT SECTION

Inactive Ingredients: Gluten-free, non-GMO, beet-derived sucrose pellets.

QUESTIONS SECTION

www.newtonlabs.net Newton Laboratories, Inc. FDA Est # 1051203 - Conyers, GA 30012
Questions? 1.800.448.7256

WARNINGS SECTION

Warning: Do not use if tamper - evident seal is broken or missing. Consult a licensed healthcare professional if pregnant, nursing or if symptoms worsen or persist for more than a few days. Keep out of reach of children.

OTC - PREGNANCY OR BREAST FEEDING SECTION

Consult a licensed healthcare professional if pregnant, nursing or if symptoms worsen or persist for more than a few days.

OTC - KEEP OUT OF REACH OF CHILDREN SECTION

Keep out of reach of children.